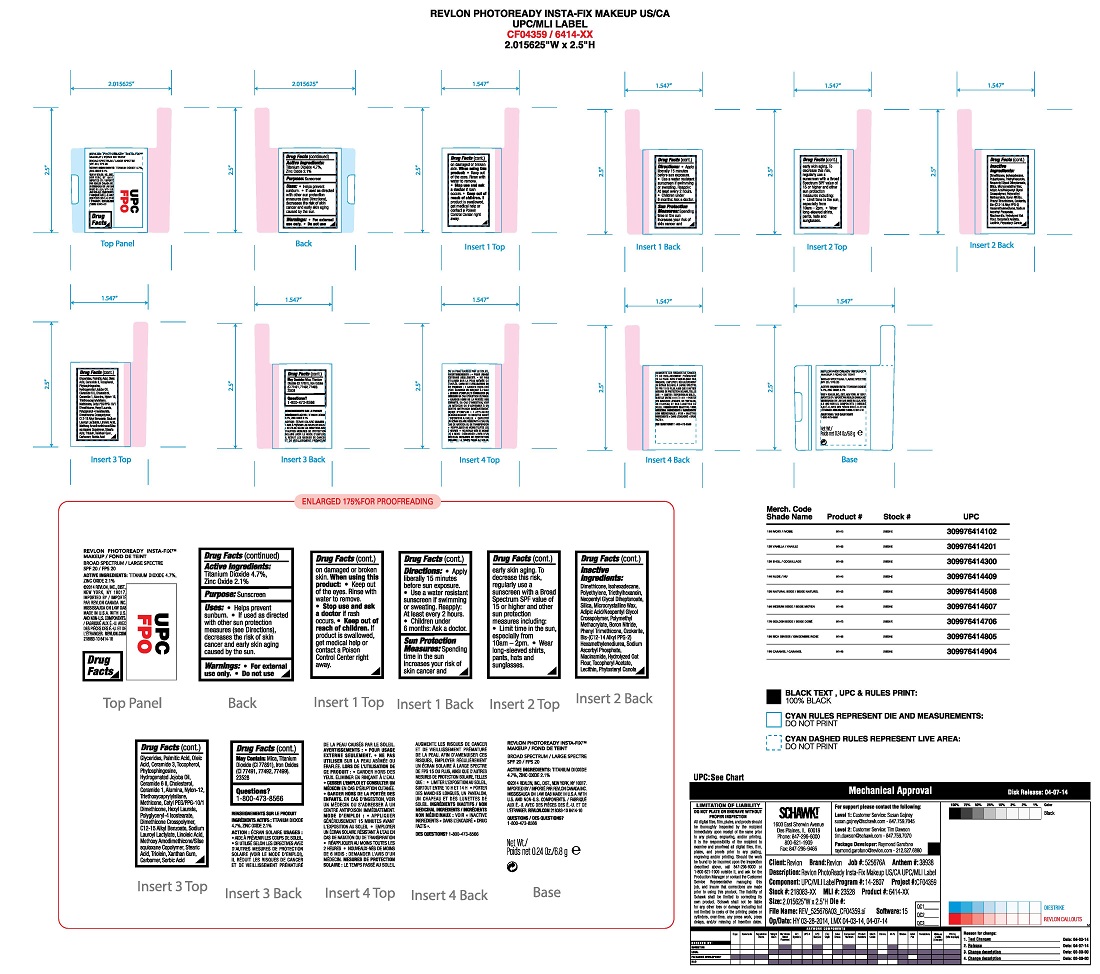 DRUG LABEL: REVLON PHOTOREADY INSTA-FIX MAKEUP
NDC: 10967-631 | Form: STICK
Manufacturer: Revlon Consumer Products Corp
Category: otc | Type: HUMAN OTC DRUG LABEL
Date: 20241231

ACTIVE INGREDIENTS: ZINC OXIDE 2.1 mg/1 mL; TITANIUM DIOXIDE 4.7 mg/1 mL
INACTIVE INGREDIENTS: DIMETHICONE; ISOHEXADECANE; HIGH DENSITY POLYETHYLENE; TRIETHYLHEXANOIN; SILICON DIOXIDE; MICROCRYSTALLINE WAX; NEOPENTYL GLYCOL DIHEPTANOATE; METHACRYLIC ACID - METHYL METHACRYLATE COPOLYMER (1:1); BORON NITRIDE; SODIUM ASCORBYL PHOSPHATE; NIACINAMIDE; OATMEAL; .ALPHA.-TOCOPHEROL ACETATE; LECITHIN, SOYBEAN; PALMITIC ACID; OLEIC ACID; TOCOPHEROL; CERAMIDE 3; PHYTOSPHINGOSINE; HYDROGENATED JOJOBA OIL; CERAMIDE 6 II; CHOLESTEROL; CERAMIDE 1; ALUMINUM OXIDE; NYLON-12; TRIETHOXYCAPRYLYLSILANE; METHICONE (20 CST); CETYL PEG/PPG-10/1 DIMETHICONE (HLB 1.5); ALKYL (C12-15) BENZOATE; SODIUM LAUROYL LACTYLATE; LINOLEIC ACID; STEARIC ACID; GLYCERYL TRIOLEATE; XANTHAN GUM; CARBOXYPOLYMETHYLENE; SORBIC ACID

REVLON PHOTOREADY INSTA-FIX MAKEUP

Active Ingredients:

Titanium Dioxide 4.3%

Zinc Oxide 2.8

Purpose:

Sunscreen

Uses:

- Helps prevent sunburn
- If used as directed with other sun protection measures (see Directions), decreases the risk of skin cancer and early skin aging caused by the sun

Warnings:

- For external use only
- Do notuse on damaged or broken skin
- When using this product: Keep out of eyes. Rinse with water to remove.
- Stop use and ask a doctor if a rash occurs
- Keep out of reach of children. If product is swallowed, get medical help or contact a Poison Control center right away

Directions:

- Apply liberally 15 minutes before sun exposure
- Use a water resistant sunscreen if swimming or sweating
- Reapply at least every 2 hours
- Children under 6 months: Ask a doctor.

Sun Protection Measures:

Spending time in the sun increases your risk of skin cancer and early skin aging. To decrease this risk, regularly use a sunscreen with a Broad Spectrum SPF value of 15 or higher and other sun protection measures including:

- Limit time in the sun, especially from 10 am - 2 pm
- Wear long-sleeved shirts, pants, hats and sunglasses.

Inactive Ingredients:

Boron Nitride, Phenyl Trimethicone, Ozokerite, Bis-(C12-14 Alkyl PPG-2) Hexamethylenediurea, Sodium Ascorbyl Phosphate, Niacinamide, Hydrolyzed Oat Flour, Tocopheryl Acetate, Lecithin, Phytosteryl Canola Glycerides, Palmitic Acid, Oleic Acid, Ceramide 3, Tocopherol, Phytosphingosine, Hydrogenated Jojoba Oil, Ceramide 6 II, Cholesterol, Ceramide 1, Alumina, Nylon-12, Triethoxycaprylylsilane, Methicone, Cetyl PEG/PPG-10/1 Dimethicone, Hexyl Laurate, Polyglyceryl-4 Isostearate, Dimethicone Crosspolymer, C12-15 Alkyl Benzoate, Sodium Lauroyl Lactylate, Linoleic Acid, Methoxy Amodimethicone/Silsesquioxane Copolymer, Stearic Acid, Triolein, Xanthan Gum, Carbomer, Sorbic Acid

May Contain Mica, Titanium Dioxide (Ci 77891), Iron Oxides (CI 77491, 77492, 77499)

DOSAGE AND ADMINISTRATION

Apply liberally 15 minutes before sun exposure.

KEEP OUT OF REACH OF CHILDREN

Keep out of the reach of children. If product is swallowed, get medical help or contact a Poison Control Center right away.

PURPOSE

Sunscreen

Principal Display Panel:

REVLON PHOTOREADY INSTA-FIX MAKEUP